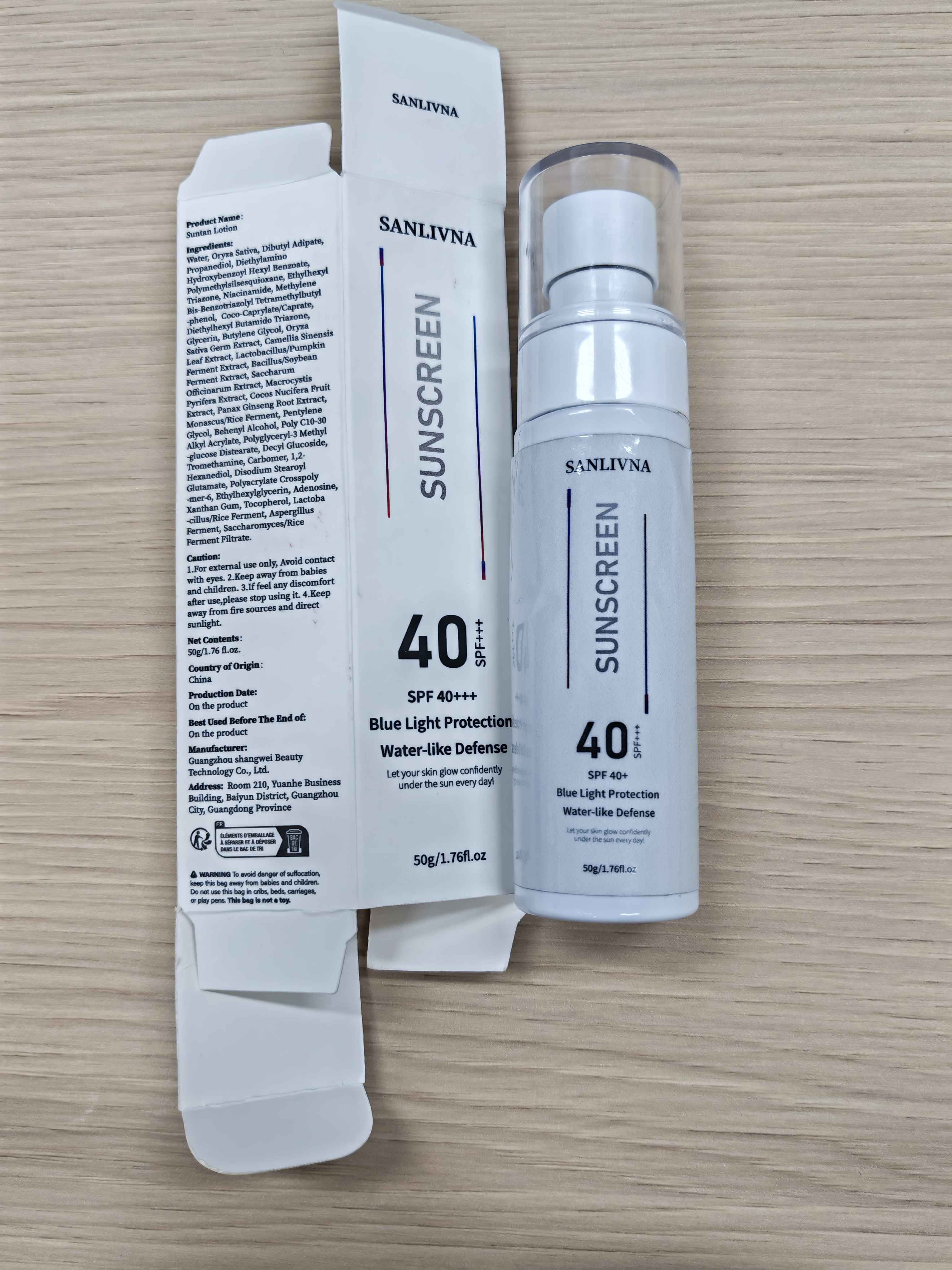 DRUG LABEL: Suntan
NDC: 85421-001 | Form: CREAM, AUGMENTED
Manufacturer: Guangzhou shangwei Beauty TechnologyCo.,Ltd.
Category: homeopathic | Type: HUMAN OTC DRUG LABEL
Date: 20250322

ACTIVE INGREDIENTS: WATER 50 g/100 1
INACTIVE INGREDIENTS: TROMETHAMINE; PENTYLENE GLYCOL; CARBOMER HOMOPOLYMER, UNSPECIFIED TYPE; ETHYLHEXYL TRIAZONE; METHYLENE BIS-BENZOTRIAZOLYL TETRAMETHYLBUTYLPHENOL; BUTYLENE GLYCOL; DECYL GLUCOSIDE; PROPANEDIOL; DIETHYLAMINO HYDROXYBENZOYL HEXYL BENZOATE; TOCOPHEROL; 1,2-HEXANEDIOL; NIACINAMIDE; POLYACRYLATE CROSSPOLYMER-6; ETHYLHEXYLGLYCERIN; POLYMETHYLSILSESQUIOXANE (11 MICRONS); DIETHYLHEXYL BUTAMIDO TRIAZONE; COCO-CAPRYLATE/CAPRATE; ORYZA SATIVA (RICE) HULL POWDER; ADENOSINE; XANTHAN GUM; DISODIUM STEAROYL GLUTAMATE; GLYCERIN; BEHENYL ALCOHOL; DIBUTYL ADIPATE

OTC-ACTIVE INGREDIENT SECTION:Water,

OTC-PURPOSR SECTION

OTC - PURPOSE SECTION

OTC-KEEP OUT OF REACH OF CHILDREN SECTION:To avoid danger of suffocation keep this bag away from babies and children Do not use this bag in cribs,beds carriages or play pens.this bag is not a toy.

INDICATIONS

1.For external use only,Avoid contact with eyes.

2.Keep away from babies and children.

3.If feel any discomfort after use，please stop using it

4.Keep away from fire sources and direct sunlight

WARNINGS SECTION

To avoid danger of suffocation keep this bag away from babies and children.Do not use this bag in cribs beds,besd,cariages,or play pens.this bag is not a toy.

DOSAGE

ERROR HAS OCCURRED 1g

INACTIVE INGREDIENT SECTION :Oryza Sativa (Rice),Dibutyl Adipate,Propanediol,Diethylamino Hydroxybenzoyl Hexyl Benzoate,Polymethylsilsesquioxane,Ethylhexyl Triazone,Niacinamide,Methylene Bis-Benzotriazolyl Tetramethylbutylphenol,Coco-Caprylate/Caprate,Diethylhexyl Butamido Triazone,Glycerin,Butylene Glycol,Decyl Glucoside,Tromethamine,Carbomer.1,2-Hexanediol,Disodium Stearoyl Glutamate,Polyacrylate Crosspolymer-6,Ethylhexylglycerin,Adenosine,Xanthan Gum,Tocopherol